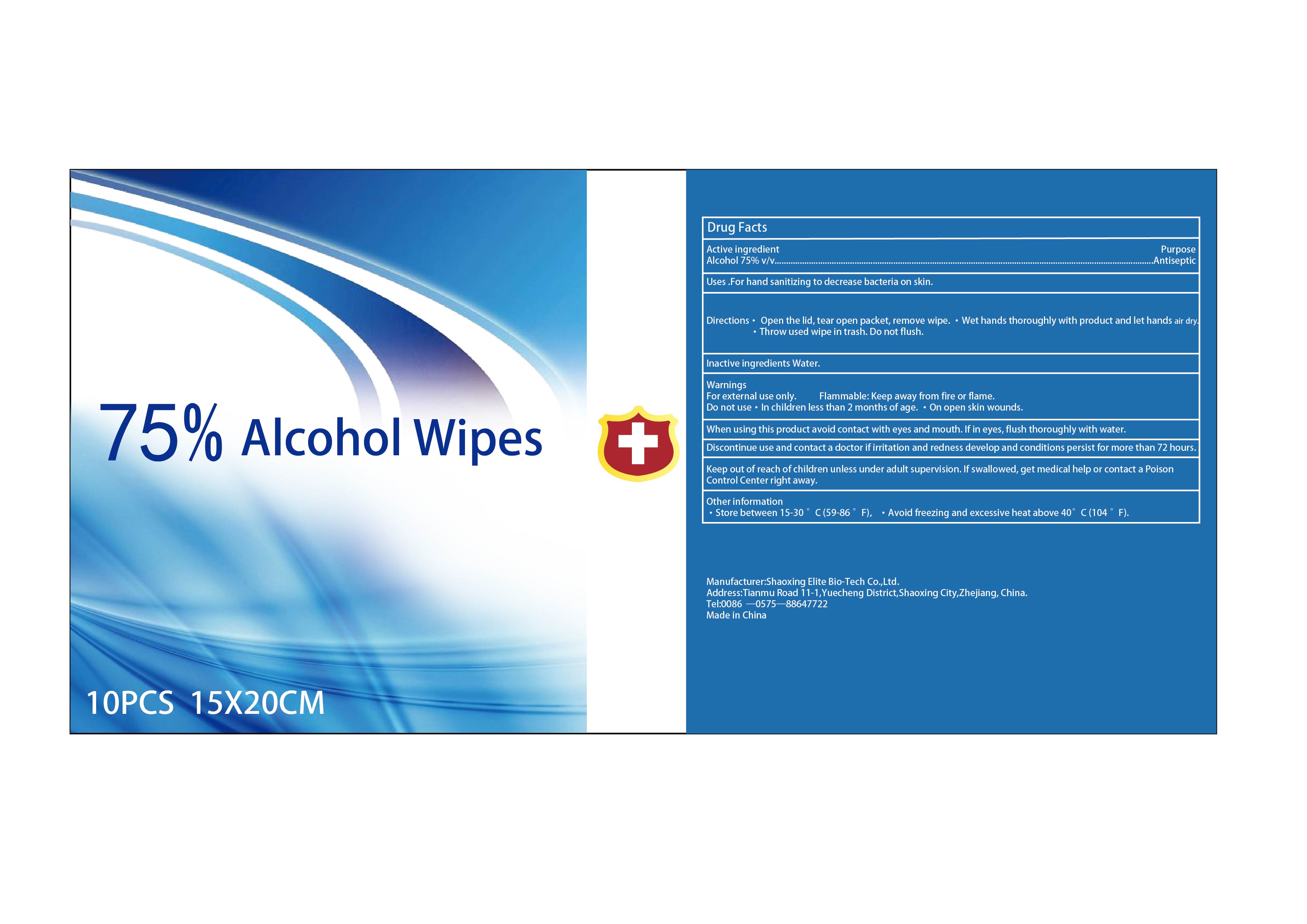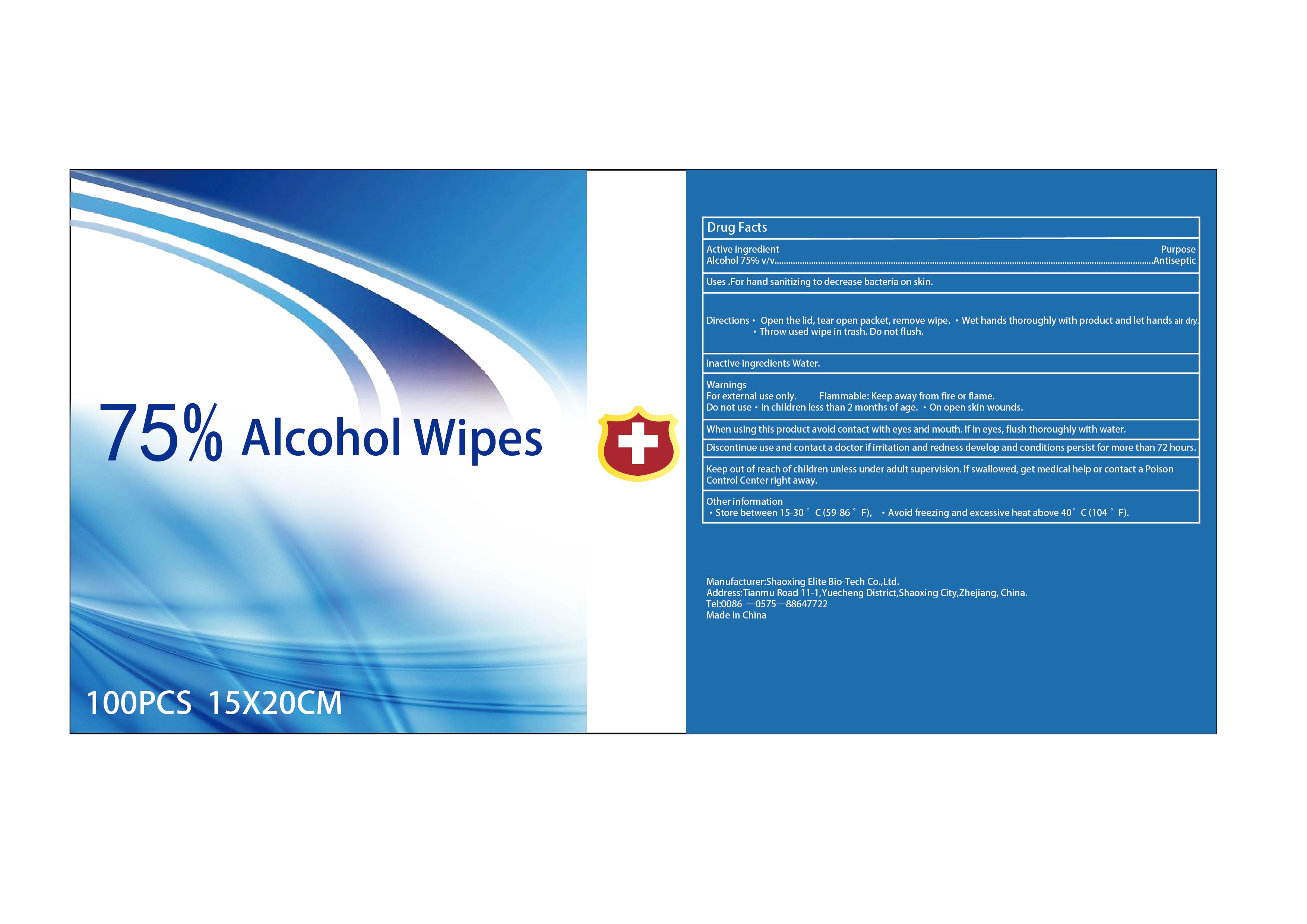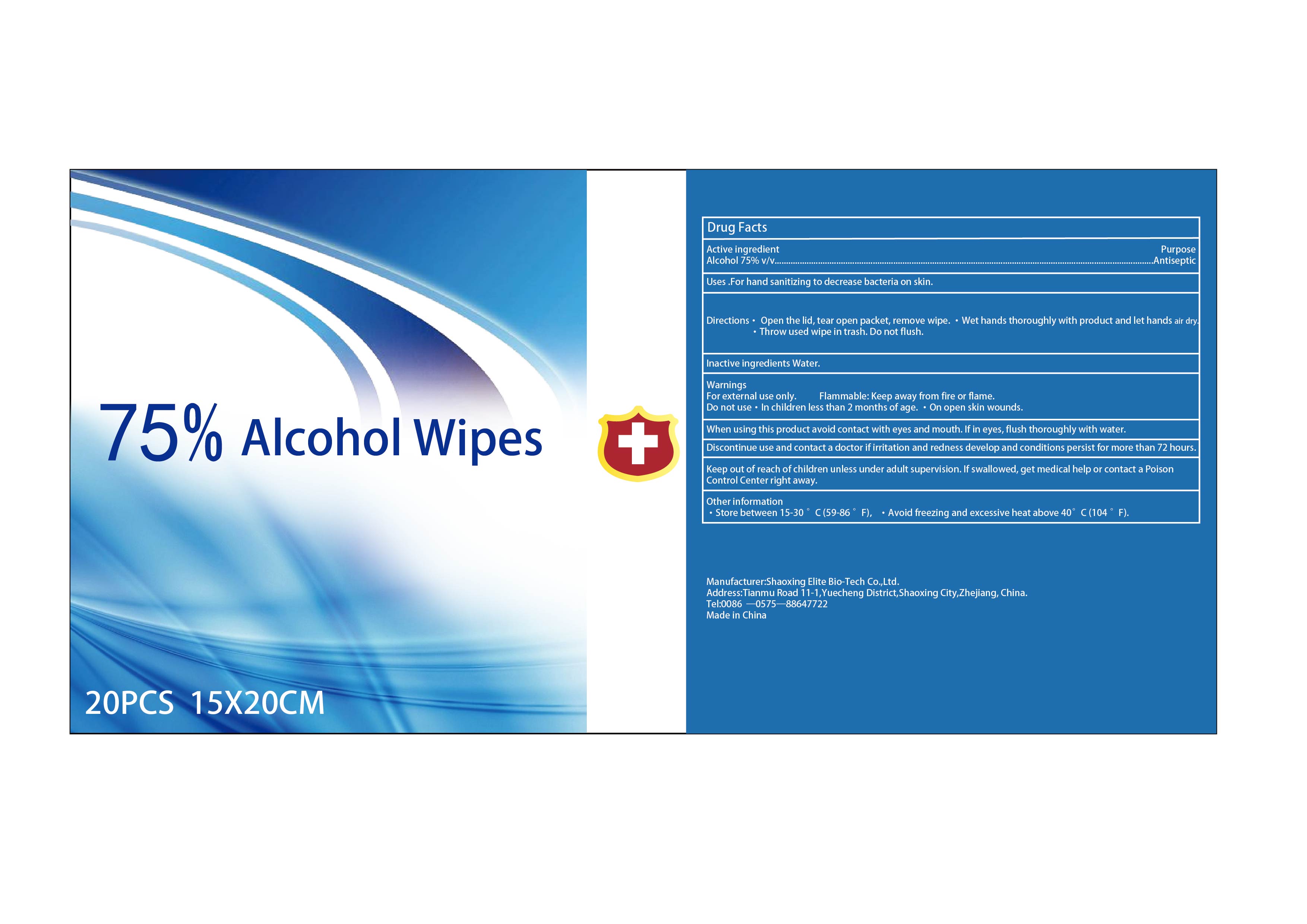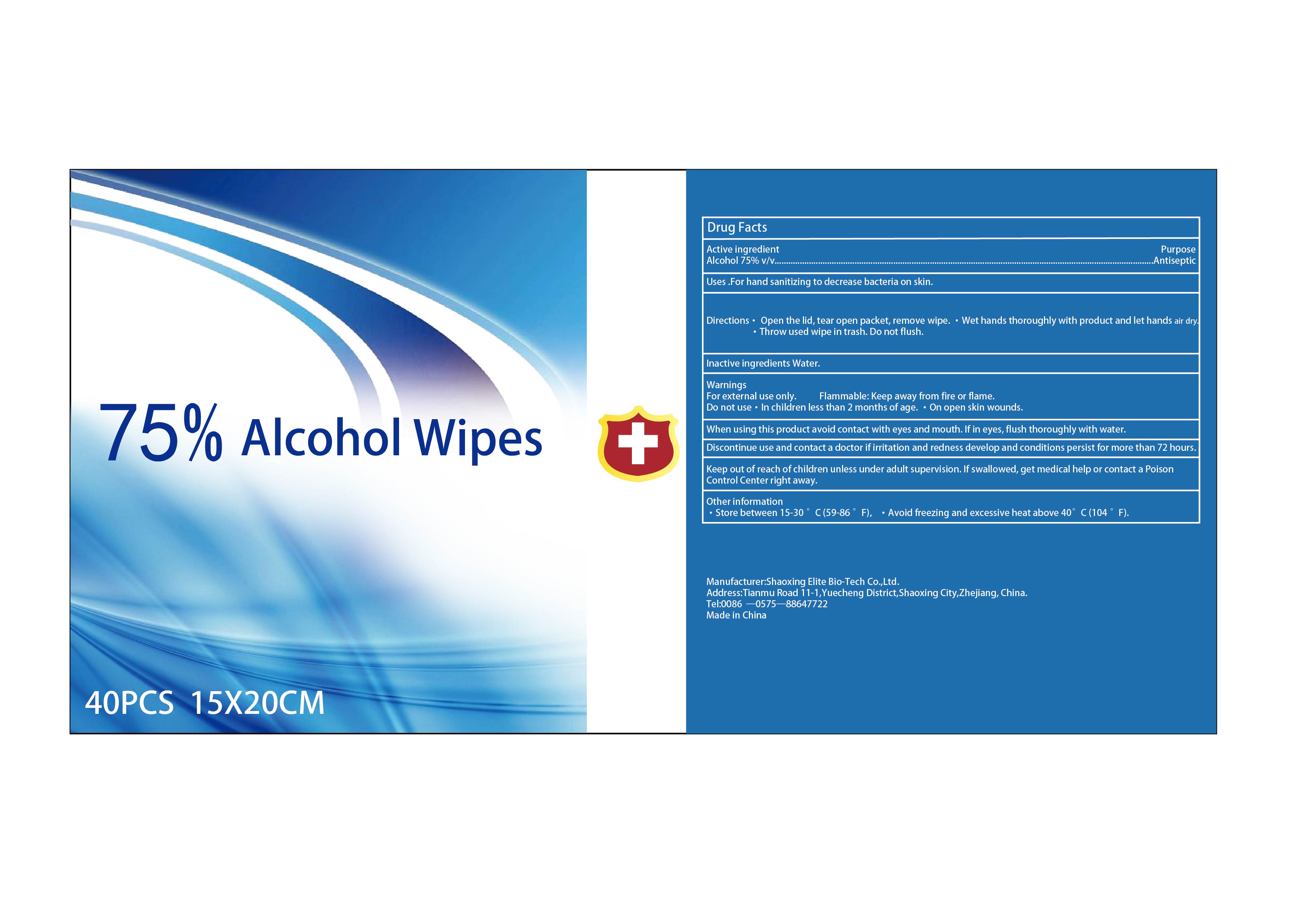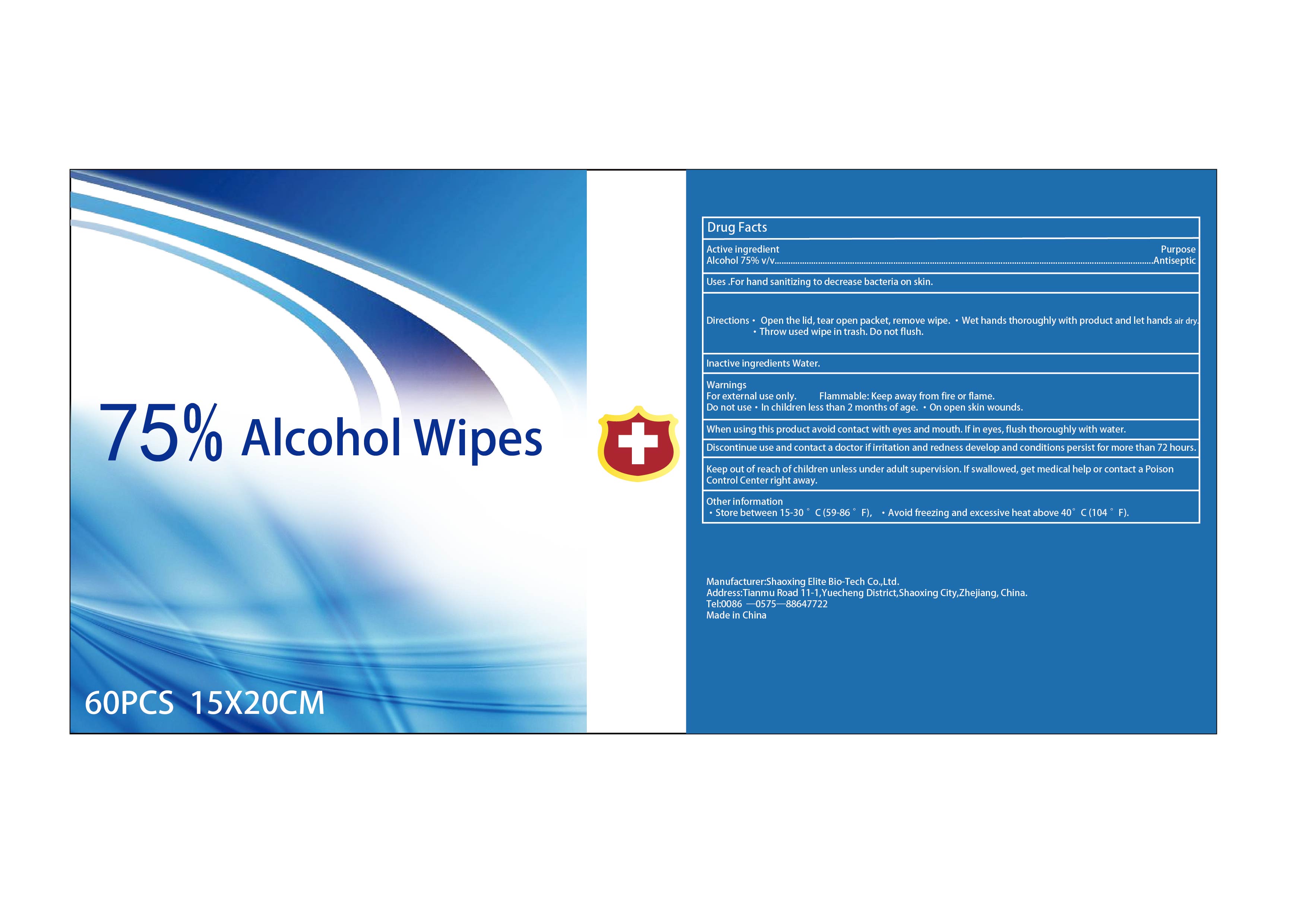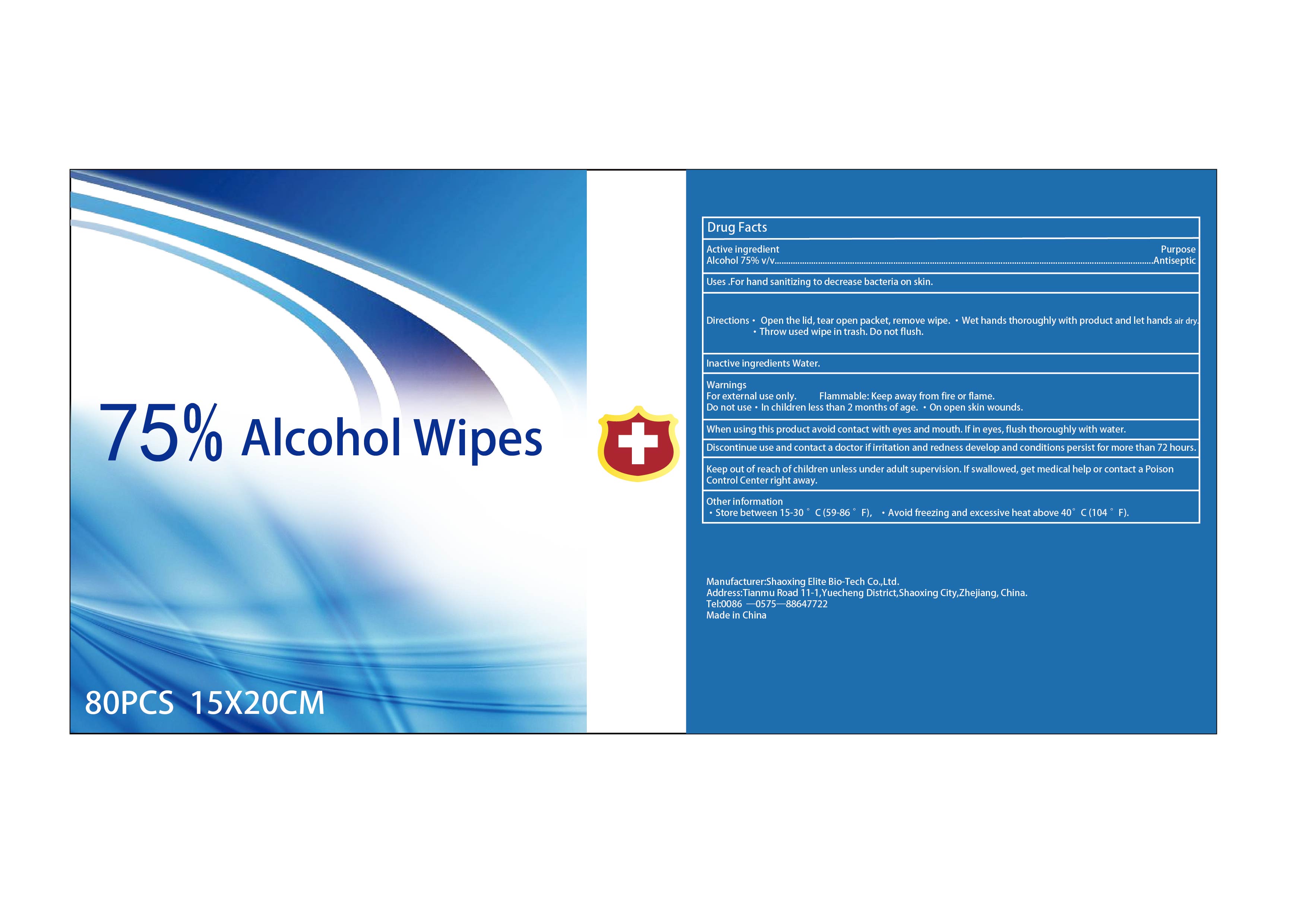 DRUG LABEL: Alcohol Wipes
NDC: 81079-002 | Form: CLOTH
Manufacturer: Shaoxing Elite Bio-Tech Co.,Ltd.
Category: otc | Type: HUMAN OTC DRUG LABEL
Date: 20231122

ACTIVE INGREDIENTS: ALCOHOL 0.75 mL/1 mL
INACTIVE INGREDIENTS: WATER

Alcohol Wipes

Drug Facts

Active Ingredient(s)

Alcohol 75% v/v

Purpose

Antiseptic

Use

For hand sanitizing to decrease bacteria on skin.

Warnings

For external use only. Flammable: Keep away from fire or flame.

Do not use

In children less than 2 months of age.

On open skin wounds.

When using this product avoid contact with eyes and mouth. If in eyes，flush thoroughly with water.

STOP USE

Discontinue use and contact a doctor if irritation and redness develop and conditions persist for more than 72 hours.

Keep out of reach of children unless under adult supervision. If swallowed, get medical help or contact a Poison Control Center right away.

Directions

Open the lid, tear open packet, remove wipe.

Wet hands thoroughly with product and let hands air dry.

Throw used wipe in trash.

Do not flush.

Other information

Store between 15-30 °C (59-86 °F).

Avoid freezing and excessive heat above 40 °C (104 °F).

Inactive ingredients

Water.

Package Label - Principal Display Panel

NDC:81079-002-01

NDC:81079-002-02

NDC:81079-002-03

NDC:81079-002-04

NDC:81079-002-05

NDC:81079-002-06